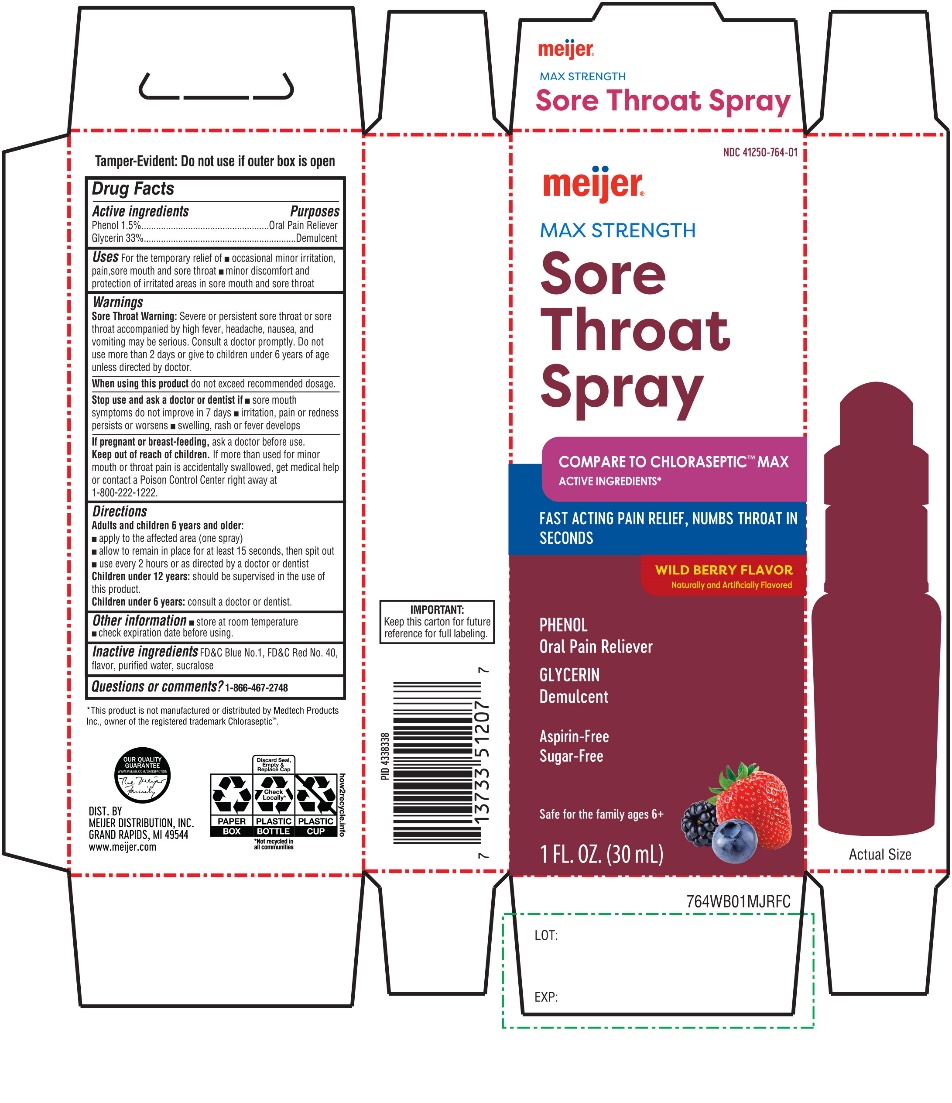 DRUG LABEL: meijer Maximum Strength Sore Throat Fast Relief
NDC: 41250-764 | Form: SPRAY
Manufacturer: MEIJER DISTRIBUTION INC
Category: otc | Type: HUMAN OTC DRUG LABEL
Date: 20251024

ACTIVE INGREDIENTS: PHENOL 15 mg/1 mL; GLYCERIN 330 mg/1 mL
INACTIVE INGREDIENTS: FD&C BLUE NO. 1; FD&C RED NO. 40; WATER; SUCRALOSE

Meijer®Sore throat spray Maximum Strength

Drug Facts

Active ingredients

Phenol 1.5%

Purpose

Oral Anesthetic/Analgesic

Active Ingredients

Glycerin 33%

Purpose

Demulcent

Uses

Temporarily:

- relieves occasional minor irritation/discomfort/pain of sore throat and sore mouth
- protects irritated areas in sore throat and sore mouth

Warnings

Sore Throat Warning:Severe or persistent sore throat or sore throat accompanied by high fever, headache, nausea, and vomiting may be serious. Consult a doctor promptly. Do not use more than 2 days or administer to children under 6 years of age unless directed by a doctor.

When using this product

do not exceed recommended dosage.

Stop Use and ask a doctor or dentist if

- sore mouth symptoms do not improve in 7 days
- irritation, pain or redness persists or worsens
- swelling, rash or fever develops

If pregnant or breast-feeding,

ask a doctor before use.

Keep out of reach of children.

In case of overdose, or accidental poisoning,get medical help or contact a Poison Control Center right away at 1-800-222-1222.

Directions

Adults and children 6 years of age and older:

- apply to the affected area (one spray)
- allow to remain in place for at least 15 seconds, then spit out
- use every 2 hours or as directed by a doctor or dentist

Children under 12 years of ageshould be supervised in the use of this product

Children under 6 years of age:consult a doctor or dentist.

Other Information

- Store at room temperature.
- Check expiration date before using

Inactive ingredients

FD&C blue #1, FD&C red #40, flavor, purified water, sucralose.

Questions or Comments?

1-866-467-2748

TAMPER- EVIDENT: DO NOT USE IF OUTER BOX IS OPEN.

PRINCIPAL DISPLAY PANEL

meijer®

NDC 41250-764-01

Compare to Chloraseptic ® Max active ingredients*

Sore Throat Spray

PHENOL 1.5%

Oral anesthetic & Analgesic

GLYCERIN 33%

Demulcent

Maximum strength

Wild Berry Flavor

Targeted spray, Coats to Protect, Aspirin, Sugar free

1FL OZ (30 mL)

*This product is not manufactured or distributed by Medtech Products Inc., a Prestige brands Co., owner of the registered trademark Chloraseptic®.

Keep this carton for future reference on full labeling.

DIST. BY MEIJER DISTRIBUTION, INC.

GRAND RAPIDS, MI 49544

www.meijer.com

MEIJER PHARMACISTS RECOMMENDED MONEY BACK GUARANTEE